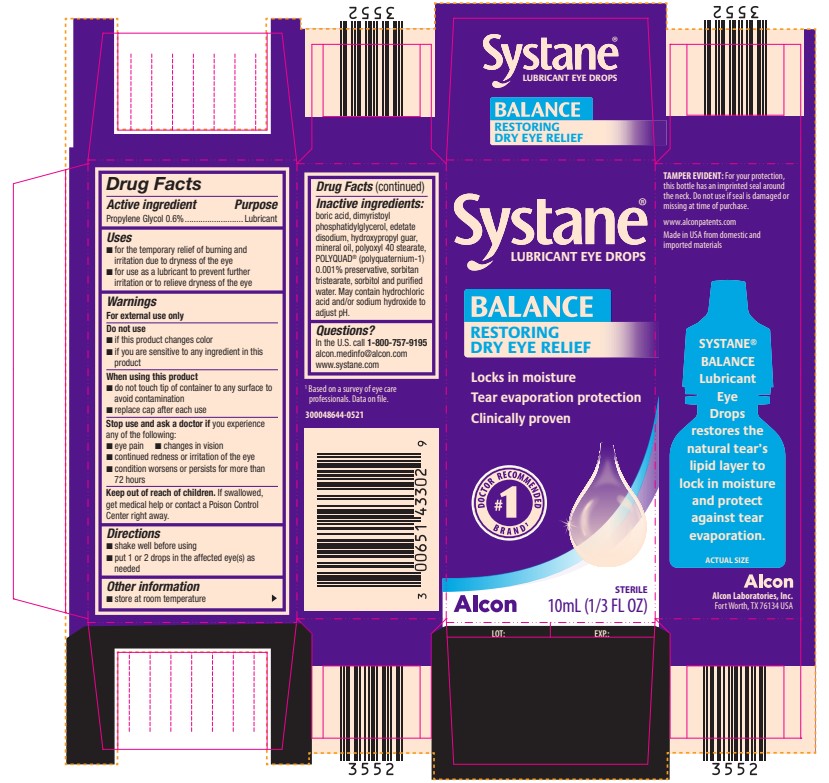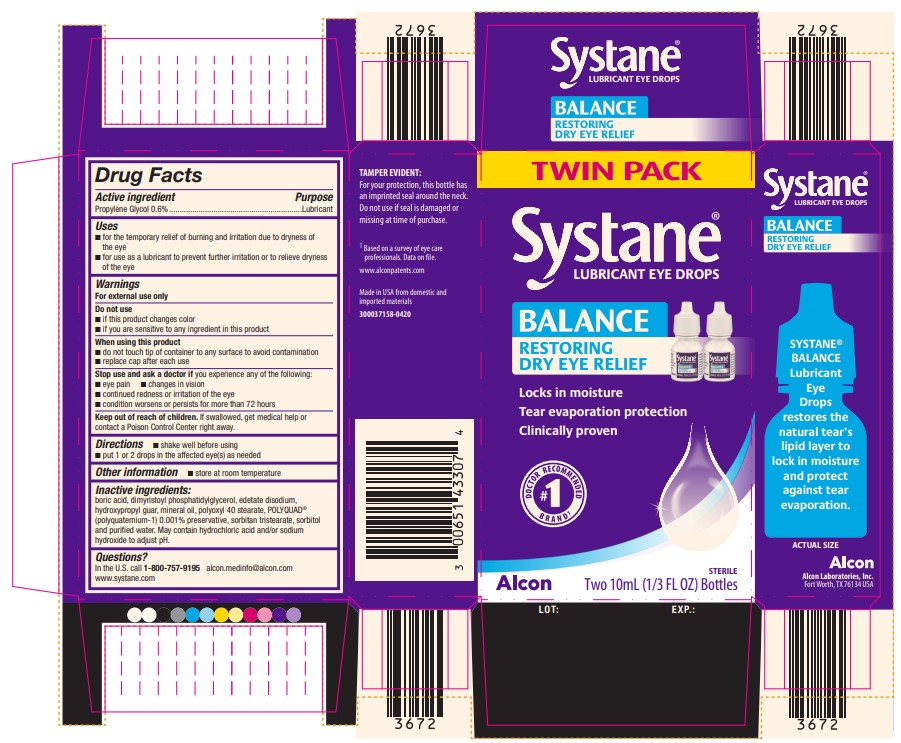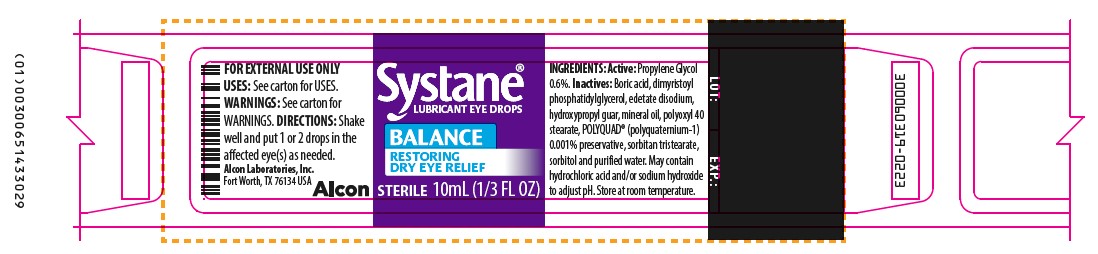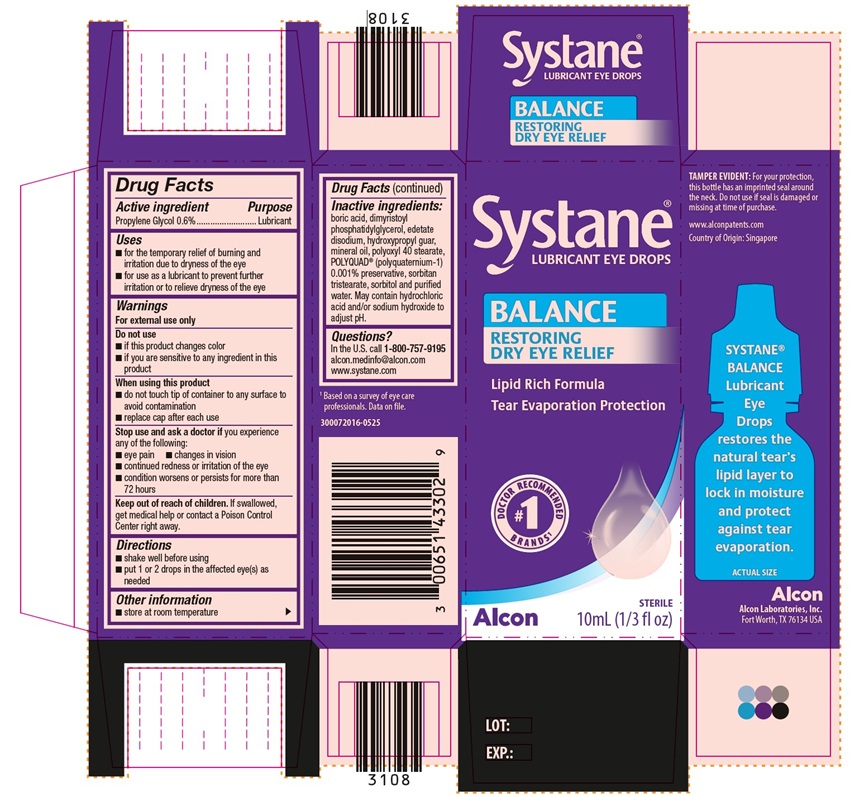 DRUG LABEL: Systane Balance
NDC: 0065-1433 | Form: EMULSION
Manufacturer: Alcon Laboratories, Inc.
Category: otc | Type: HUMAN OTC DRUG LABEL
Date: 20250807

ACTIVE INGREDIENTS: Propylene Glycol 0.06 mg/1 mL
INACTIVE INGREDIENTS: Boric Acid; Dimyristoylphosphatidylglycerol, Dl-; Edetate Disodium; Guar Gum; Mineral Oil; Polyoxyl 40 Stearate; Sorbitan Tristearate; Sorbitol; Water; Hydrochloric Acid; Sodium Hydroxide; Polidronium Chloride

SYSTANE® BALANCE Lubricant Eye Drops

ACTIVE INGREDIENT

Active Ingredient | Purpose
Propylene Glycol 0.6% | Lubricant

Uses

- for the temporary relief of burning and irritation due to dryness of the eye
- for use as a lubricant to prevent further irritation or to relive dryness of the eye

Warnings

For external use only

Do not use

- if this product changes color
- if you are sensitive to any ingredient in this product

When using this product

- do not touch tip of container to any surface to avoid contamination
- replace cap after each use

Stop use and ask a doctor if you experience any of the following:

- eye pain
- changes in vision
- continued redness or irritation of the eye
- condition worsens or persists for more than 72 hours

Keep out of reach of children. If swallowed, get medical help or contact a Poison Control Center right away.

Directions

- shake well before using
- put 1 or 2 drops in the affected eye(s) as needed

Other information

- store at room temperature

Inactive ingredients:

boric acid, dimyristoyl phosphatidylglycerol, edetate disodium, hydroxypropyl guar, mineral oil, polyoxyl 40 stearate, POLYQUAD® (polyquaternium-1) 0.001% preservative, sorbitan tristearate, sorbitol and purified water. May contain hydrochloric acid and/or sodium hydroxide to adjust pH.

Questions:

In the U.S. call 1-800-757-9195
alcon.medinfo@alcon.com
www.systane.com

PRINCIPAL DISPLAY PANEL

Systane®
LUBRICANT EYE DROPS
BALANCE
Restoring
Dry Eye Relief
Locks in moisture
Tear evaporation protection
Clinically proven
DOCTOR RECOMMENDED #1 BRAND^1
Alcon
STERILE
10 mL (1/3 FL OZ)
LOT: EXP.:

SIDE PANEL
TAMPER EVIDENT: For your protection,
this bottle has an imprinted seal around
the neck. Do not use if seal is damaged or
missing at time of purchase.
www.alconpatents.com
Made in USA from domestic and
imported materials
Systane®
BALANCE
Lubricant
Eye
Drops
restores the
natural tear’s
lipid layer to
lock in moisture
and protect
against tear
evaporation.
ACTUAL SIZE
Alcon
Alcon Laboratories, Inc.
Fort Worth, TX 76134 USA
^1 Based on a survey of eye care
professionals. Data on file.
300048644-0521

PRINCIPAL DISPLAY PANEL

TWIN PACK
Systane®
LUBRICANT EYE DROPS
BALANCE
Restoring
Dry Eye Relief
Locks in moisture
Tear evaporation protection
Clinically proven
DOCTOR RECOMMENDED #1 BRAND^1
Alcon
STERILE
Two 10 mL (1/3 FL OZ) Bottles
LOT: EXP.:
SIDE PANEL
TAMPER EVIDENT: For your protection, this bottle has an imprinted seal around the neck. Do not use if seal is damaged or missing at time of purchase.
www.alconpatents.com
Made in USA from domestic and
imported materials
Systane® BALANCE Lubricant Eye Drops restores the natural tear’s lipid layer to lock in moisture and protect against tear evaporation.
ACTUAL SIZE
Alcon
Alcon Laboratories, Inc.
Fort Worth, TX 76134 USA
^1 Based on a survey of eye care
professionals. Data on file.
300037158-0420

Systane®
LUBRICANT EYE DROPS
BALANCE
Restoring
Dry Eye Relief
Lipid Rich Formula
Tear evaporation protection
DOCTOR RECOMMENDED #1 BRANDS^1
Alcon
STERILE
10 mL (1/3 fl oz)
LOT: EXP.:
SIDE PANEL
TAMPER EVIDENT: For your protection,
this bottle has an imprinted seal around
the neck. Do not use if seal is damaged or
missing at time of purchase.
www.alconpatents.com
Country of Origin: Singapore
Systane®
BALANCE
Lubricant
Eye
Drops
restores the
natural tear’s
lipid layer to
lock in moisture
and protect
against tear
evaporation.
ACTUAL SIZE
Alcon
Alcon Laboratories, Inc.
Fort Worth, TX 76134 USA
^1Based on a survey of eye care professionals. Data on file.
300072016-0525

PRINCIPAL DISPLAY PANEL

Systane®
LUBRICANT EYE DROPS
BALANCE
Restoring
Dry Eye Relief
STERILE
10 mL (1/3 FL OZ)
INGREDIENTS: Active: Propylene Glycol 0.6%. Inactives: Boric acid, dimyristoyl phosphatidylglycerol, edetate disodium, hydroxypropyl guar, mineral oil, polyoxyl 40
stearate, POLYQUAD® (polyquaternium-1) 0.001% preservative, sorbitan tristearate, sorbitol and purified water. May contain hydrochloric acid and/or sodium hydroxide to
adjust pH. Store at room temperature.
FOR EXTERNAL USE ONLY
USES: See carton for USES.
WARNINGS: See carton for WARNINGS.
DIRECTIONS: Shake well and put 1 or 2 drops in the affected eye(s) as needed.
Alcon
Alcon Laboratories, Inc.
Fort Worth, TX 76134 USA
300060319-0223